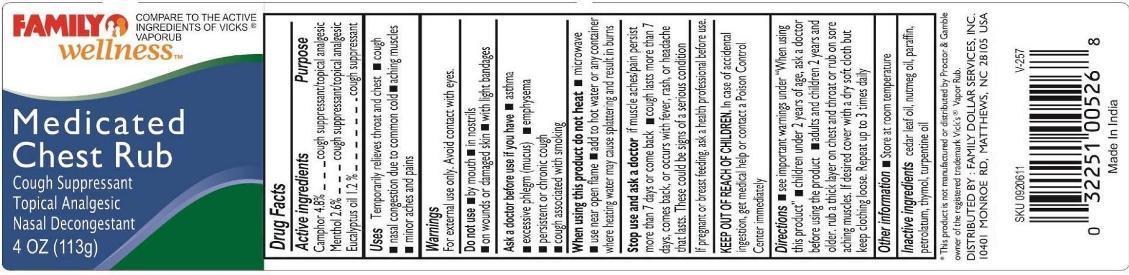 DRUG LABEL: MEDICATED CHEST RUB
NDC: 55319-102 | Form: CREAM
Manufacturer: Family Dollar Services Inc
Category: otc | Type: HUMAN OTC DRUG LABEL
Date: 20131106

ACTIVE INGREDIENTS: CAMPHOR (SYNTHETIC) 4.8 g/100 g; MENTHOL 2.6 g/100 g; EUCALYPTUS OIL 1.2 g/100 g
INACTIVE INGREDIENTS: CEDAR LEAF OIL; NUTMEG OIL; PARAFFIN; PETROLATUM; THYMOL; TURPENTINE OIL

MEDICATED CHEST RUB

Active ingredients

Camphor 4.8%
Menthol 2.6%
Eucalyptus oil 1.2%

Purpose

Cough suppressant /topical analgesic

Cough suppressant /topical analgesic

Cough supressant

Uses

Temporarily relieves throat and chest

- cough
- nasal congestion due to common cold
- aching muscles
- minor aches and pains

Warnings

For external use only. Avoid contact with eyes

Do not use

- by mouth
- in nostrils
- on wounds or damaged skin
- with light bandages

Ask a doctor before use if you have

- asthma
- excessive phlegm (mucus)
- emphysema
- persistent or chronic cough
- cough associated with smoking

When using this product do not heat

- microwave
- use near open flame
- add to hot water or any container where heating water may cause splattering and result in burns

Stop use and ask a doctor if

- muscle aches/pain persist more than more than 7 days or come back
- cough lasts more than 7 days, comes back, or occurs with fever, rash, or headache that lasts. These could be signs of a serious condition.

PREGNANCY OR BREAST FEEDING

If pregnant or breast feeding, ask a health professional before use

Keep out of reach of children.

In case of accidental ingestion get medical help or contact a Poison Control Center immediately.

Directions

- see important warnings under "When using this product"
- children under 2 years of age, ask a doctor before using the product
- adults and children 2 years and older, rub a thick layer on chest and throat or rub on sore, aching muscles. If desired cover with a dry soft cloth but keep clothing loose. Repeat up to 3 times daily

Other information

Store at room temperature

Inactive ingredients

cedar leaf oil, nutmeg oil, paraffin, petrolatum, thymol, turpentine oil

PRINCIPAL DISPLAY PANEL